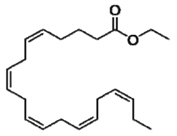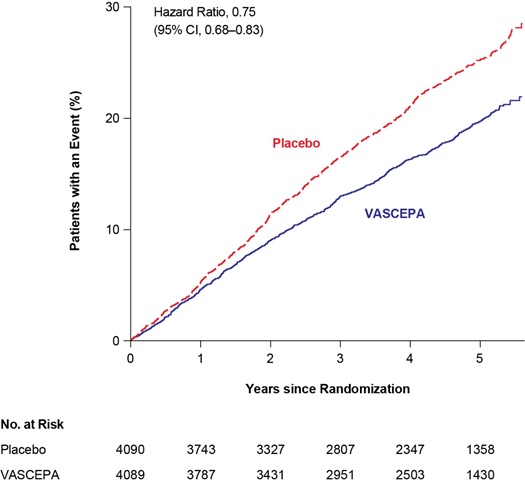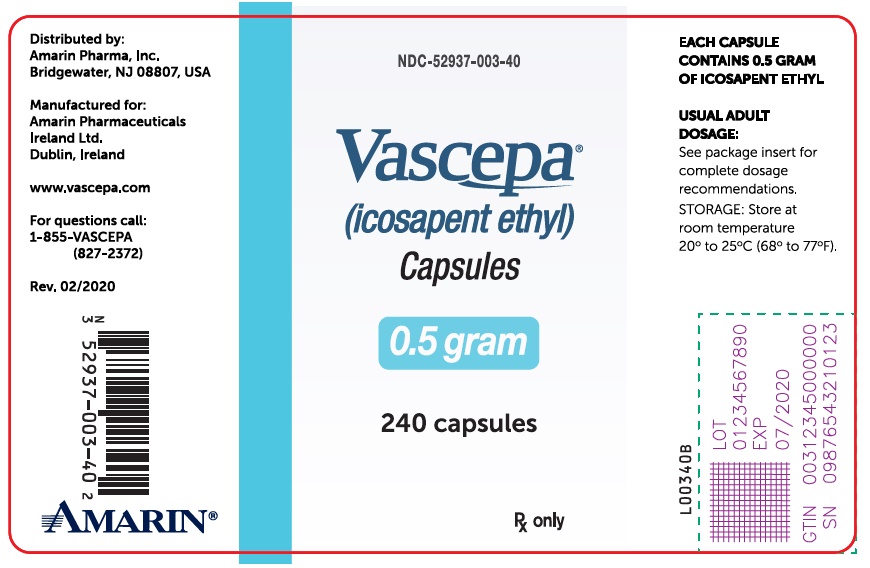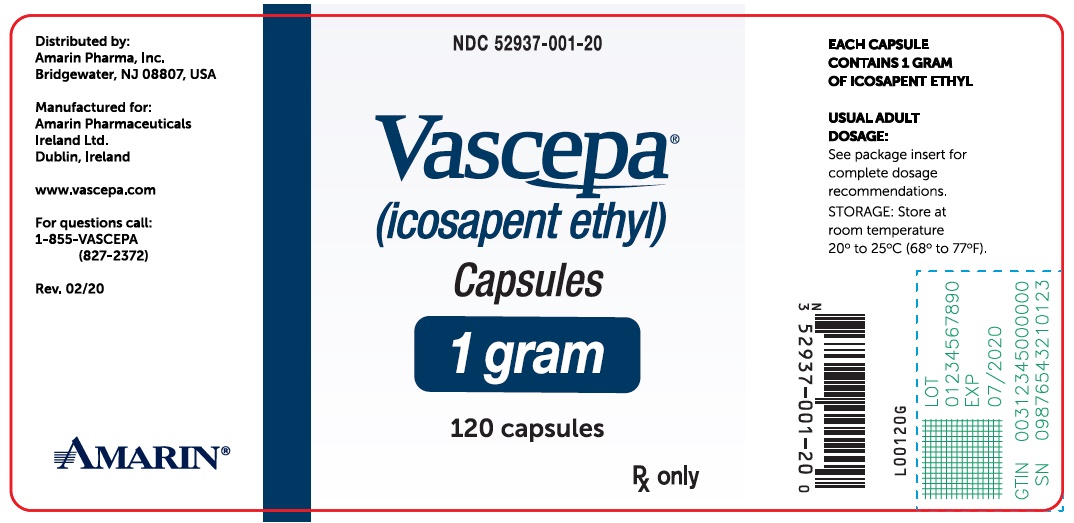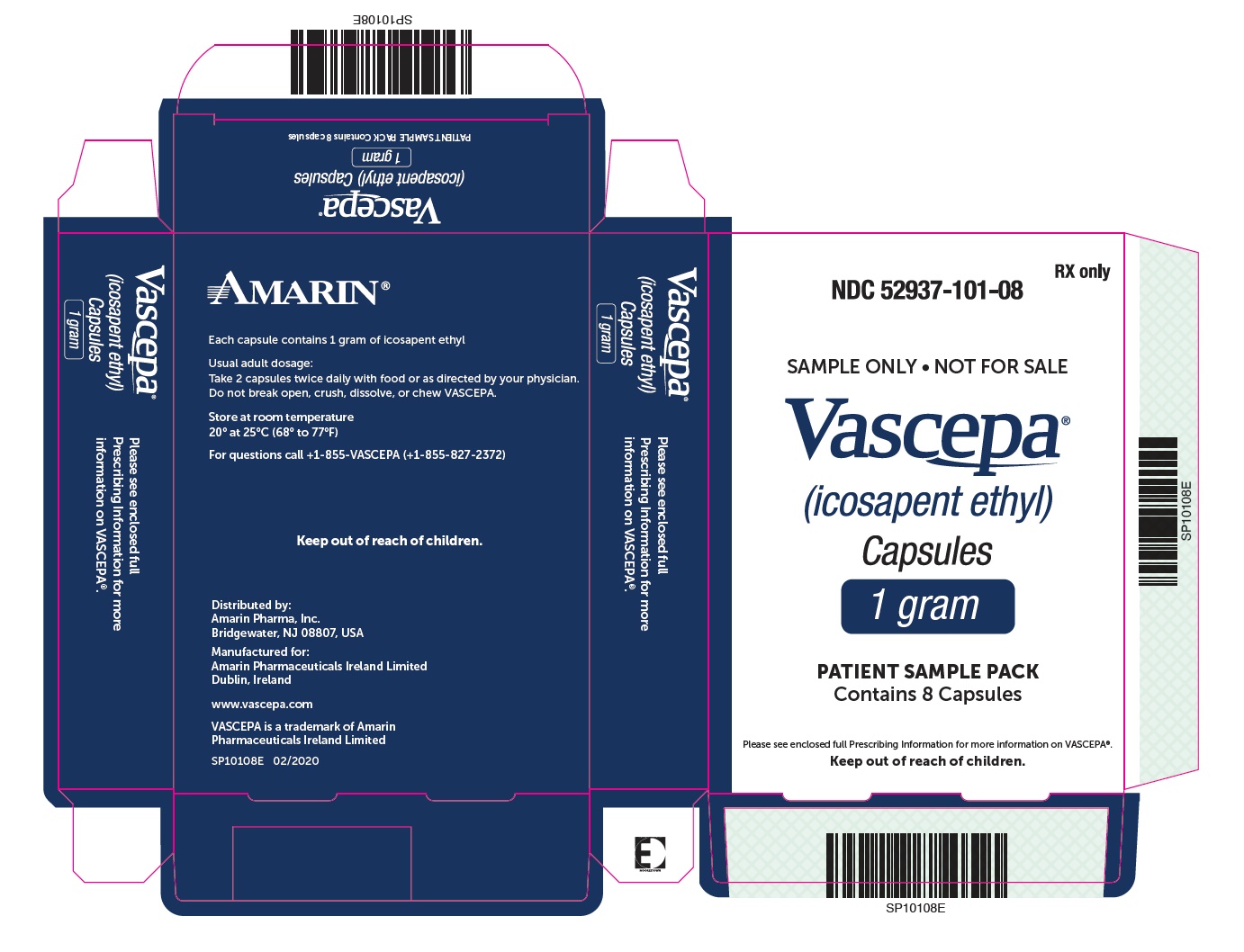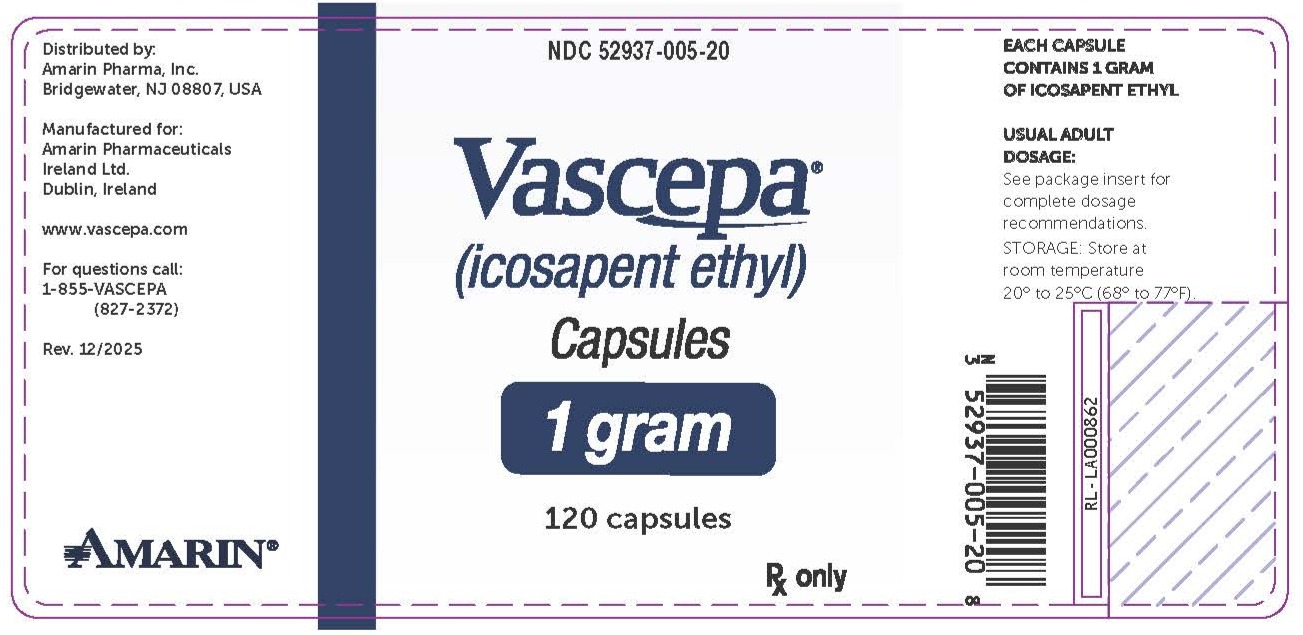 DRUG LABEL: Vascepa
NDC: 52937-001 | Form: CAPSULE
Manufacturer: Amarin Pharma Inc.
Category: prescription | Type: HUMAN PRESCRIPTION DRUG LABEL
Date: 20251216

ACTIVE INGREDIENTS: icosapent ethyl 1000 mg/1 1
INACTIVE INGREDIENTS: Tocopherol 2 mg/1 1; Gelatin, Unspecified; Sorbitol; Glycerin; Maltitol; Water

HIGHLIGHTS OF PRESCRIBING INFORMATION

These highlights do not include all the information needed to use VASCEPA® safely and effectively. See full prescribing information for VASCEPA.
VASCEPA® (icosapent ethyl) capsules, for oral use
Initial U.S. Approval: 2012

1 INDICATIONS AND USAGE

VASCEPA is an ethyl ester of eicosapentaenoic acid (EPA) indicated:

- as an adjunct to maximally tolerated statin therapy to reduce the risk of myocardial infarction, stroke, coronary revascularization, and unstable angina requiring hospitalization in adult patients with elevated triglyceride (TG) levels(≥ 150 mg/dL) and
  - established cardiovascular disease or
  - diabetes mellitus and 2 or more additional risk factors for cardiovascular disease. (1)
- as an adjunct to diet to reduce TG levels in adult patients with severe (≥ 500 mg/dL) hypertriglyceridemia. (1)

Limitations of Use:

- The effect of VASCEPA on the risk for pancreatitis in patients with severe hypertriglyceridemia has not been determined. (1)

2 DOSAGE AND ADMINISTRATION

- Assess lipid levels before initiating therapy. Identify other causes of high triglyceride levels and manage as appropriate. (2.1)
- Patients should engage in appropriate nutritional intake and physical activity before receiving VASCEPA, which should continue during treatment. (2.1)
- The daily dose of VASCEPA is 4 grams per day taken as either
  - four 0.5 gram capsules twice daily with food or
  - two 1 gram capsules twice daily with food. (2.2)
- Advise patients to swallow capsules whole. Do not break open, crush, dissolve, or chew VASCEPA. (2.2)

3 DOSAGE FORMS AND STRENGTHS

Capsules: 0.5 gram and 1 gram (3)

4 CONTRAINDICATIONS

VASCEPA is contraindicated in patients with known hypersensitivity (e.g., anaphylactic reaction) to VASCEPA or any of its components. (4)

5 WARNINGS AND PRECAUTIONS

Atrial Fibrillation/Flutter: VASCEPA was associated with an increased risk of atrial fibrillation or atrial flutter requiring hospitalization in a double-blind, placebo-controlled trial. The incidence of atrial fibrillation was greater in patients with a previous history of atrial fibrillation or atrial flutter. (5.1)

Potential for Allergic Reactions in Patients with Fish Allergy: VASCEPA contains ethyl esters of the omega-3 fatty acid, eicosapentaenoic acid (EPA), obtained from the oil of fish. It is not known whether patients with allergies to fish and/or shellfish are at increased risk of an allergic reaction to VASCEPA. Inform patients with known hypersensitivity to fish and/or shellfish about the potential for allergic reactions and advise them to discontinue VASCEPA and seek medical attention if any reactions occur. (5.2)

Bleeding: VASCEPA was associated with an increased risk of bleeding in a double-blind, placebo-controlled trial. The incidence of bleeding was greater in patients receiving concomitant antithrombotic medications, such as aspirin, clopidogrel, or warfarin. (5.3)

6 ADVERSE REACTIONS

Common adverse reactions in the cardiovascular outcomes trial (incidence ≥3% and ≥1% more frequent than placebo): musculoskeletal pain, peripheral edema, constipation, gout, and atrial fibrillation (6.1)

Common adverse reactions in the hypertriglyceridemia trials (incidence ≥1% more frequent than placebo): arthralgia and oropharyngeal pain. (6.1)

To report SUSPECTED ADVERSE REACTIONS, contact Amarin Pharma, Inc. at 1-855-VASCEPA (1-855-827-2372) or contact the FDA at 1-800-FDA-1088 or www.fda.gov/medwatch.

7 DRUG INTERACTIONS

Increased Bleeding Risk with Anticoagulants and Antiplatelet Agents: Some published studies with omega-3 fatty acids have demonstrated prolongation of bleeding time. Monitor patients receiving VASCEPA and concomitant anticoagulants and/or antiplatelet agents for bleeding. (7)

FULL PRESCRIBING INFORMATION

1 INDICATIONS AND USAGE

VASCEPA® (icosapent ethyl) is indicated:

- as an adjunct to maximally tolerated statin therapy to reduce the risk of myocardial infarction, stroke, coronary revascularization, and unstable angina requiring hospitalization in adult patients with elevated triglyceride (TG) levels (≥ 150 mg/dL) and
  - established cardiovascular disease or
  - diabetes mellitus and 2 or more additional risk factors for cardiovascular disease.
- as an adjunct to diet to reduce TG levels in adult patients with severe (≥ 500 mg/dL) hypertriglyceridemia.

Limitations of Use:

The effect of VASCEPA on the risk for pancreatitis in patients with severe hypertriglyceridemia has not been determined.

2 DOSAGE AND ADMINISTRATION

2.1 Prior to Initiation of VASCEPA

- Assess lipid levels before initiating therapy. Identify other causes (e.g., diabetes mellitus, hypothyroidism, or medications) of high triglyceride levels and manage as appropriate.
- Patients should engage in appropriate nutritional intake and physical activity before receiving VASCEPA, which should continue during treatment with VASCEPA.

2.2 Dosage and Administration

- The daily dose of VASCEPA is 4 grams per day taken as either:
  - four 0.5 gram capsules twice daily with food; or as
  - two 1 gram capsules twice daily with food.
- Advise patients to swallow VASCEPA capsules whole. Do not break open, crush, dissolve, or chew VASCEPA.

3 DOSAGE FORMS AND STRENGTHS

VASCEPA capsules are supplied as:

- 0.5 gram amber-colored, oval, soft-gelatin capsules imprinted with V500
- 1 gram amber-colored, oblong, soft-gelatin capsules imprinted with VASCEPA
- 1 gram amber-colored, oblong, soft-gelatin capsules imprinted with IPE

4 CONTRAINDICATIONS

VASCEPA is contraindicated in patients with known hypersensitivity (e.g., anaphylactic reaction) to VASCEPA or any of its components.

5 WARNINGS AND PRECAUTIONS

5.1 Atrial Fibrillation/Flutter

VASCEPA is associated with an increased risk of atrial fibrillation or atrial flutter requiring hospitalization. In a double-blind, placebo-controlled trial of 8,179 statin-treated subjects with established cardiovascular disease (CVD) or diabetes plus an additional risk factor for CVD, adjudicated atrial fibrillation or atrial flutter requiring hospitalization for 24 or more hours occurred in 127 (3%) patients treated with VASCEPA compared to 84 (2%) patients receiving placebo [HR= 1.5 (95% CI 1.14, 1.98)]. The incidence of atrial fibrillation was greater in patients with a previous history of atrial fibrillation or atrial flutter.

5.2 Potential for Allergic Reactions in Patients with Fish Allergy

VASCEPA contains ethyl esters of the omega-3 fatty acid, eicosapentaenoic acid (EPA), obtained from the oil of fish. It is not known whether patients with allergies to fish and/or shellfish are at increased risk of an allergic reaction to VASCEPA. Inform patients with known hypersensitivity to fish and/or shellfish about the potential for allergic reactions to VASCEPA and advise them to discontinue VASCEPA and seek medical attention if any reactions occur.

5.3 Bleeding

VASCEPA is associated with an increased risk of bleeding. In a double-blind, placebo-controlled cardiovascular outcomes trial of 8,179 patients, 482 (12%) patients receiving VASCEPA experienced a bleeding event compared to 404 (10%) patients receiving placebo. Serious bleeding events occurred in 111 (3%) of patients on VASCEPA vs. 85 (2%) of patients receiving placebo. The incidence of bleeding was greater in patients receiving concomitant antithrombotic medications, such as aspirin, clopidogrel, or warfarin.

6 ADVERSE REACTIONS

The following important adverse reactions are described below and elsewhere in the labeling:

- Atrial Fibrillation or Atrial Flutter [see Warnings and Precautions (5.1)]
- Potential for Allergic Reactions in Patients with Fish Allergy [see Warnings and Precautions (5.2)]
- Bleeding [see Warnings and Precautions (5.3)]

6.1 Clinical Trials Experience

Because clinical trials are conducted under widely varying conditions, adverse reaction rates observed in the clinical trials of a drug cannot be directly compared to rates in the clinical trials of another drug and may not reflect the rates observed in practice.

Cardiovascular Outcomes Trial

In a double-blind, randomized, placebo-controlled cardiovascular outcomes trial, 8,179 statin-stabilized patients were randomized to receive VASCEPA or placebo and followed for a median of 4.9 years [see Clinical Studies (14.1)]. The median age at baseline was 64 years, 29% were women, 90% White, 5% Asian, 2% were Black, and 4% identified as Hispanic ethnicity.

Common adverse reactions (incidence ≥3% on VASCEPA and ≥1% more frequent than placebo) included musculoskeletal pain, peripheral edema, constipation, gout, and atrial fibrillation.

Hypertriglyceridemia Trials

In two randomized, double-blind, placebo-controlled trials in patients with triglyceride levels between 200 and 2000 mg/dL treated for 12 weeks, adverse reactions reported with VASCEPA at an incidence ≥1% more frequent than placebo based on pooled data included arthralgia and oropharyngeal pain.

6.2 Postmarketing Experience

Additional adverse reactions have been identified during post-approval use of VASCEPA. Because these reactions are reported voluntarily from a population of uncertain size, it is generally not possible to reliably estimate their frequency or establish a causal relationship to drug exposure.

- Diarrhea
- Blood triglycerides increased
- Abdominal discomfort
- Pain in the extremities

7 DRUG INTERACTIONS

7.1 Increased Bleeding Risk with Anticoagulants and Antiplatelet Agents

Some published studies with omega-3 fatty acids have demonstrated prolongation of bleeding time. The prolongation of bleeding time reported in those studies has not exceeded normal limits and did not produce clinically significant bleeding episodes. Monitor patients receiving VASCEPA and concomitant anticoagulants and/or antiplatelet agents for bleeding.

8 USE IN SPECIFIC POPULATIONS

8.1 Pregnancy

Risk Summary

The available data from published case reports and the pharmacovigilance database on the use of VASCEPA in pregnant women are insufficient to identify a drug-associated risk for major birth defects, miscarriage or adverse maternal or fetal outcomes. In animal reproduction studies in pregnant rats, non-dose-related imbalances for some minor developmental findings were observed with oral administration of icosapent ethyl during organogenesis at exposures that were equivalent to the clinical exposure at the human dose of 4 g/day, based on body surface area comparisons. In a study in pregnant rabbits orally administered icosapent ethyl during organogenesis, there were no clinically relevant adverse developmental effects at exposures that were 5 times the clinical exposure, based on body surface area comparisons (see Data).

The estimated background risk of major birth defects and miscarriage for the indicated population is unknown. All pregnancies have a background risk of birth defect, loss, or other adverse outcomes. In the U.S. general population, the estimated background risk of major birth defects and miscarriage in clinically recognized pregnancies is 2-4% and 15-20%, respectively.

Data

Animal Data

In pregnant rats given oral gavage doses of 0.3, 1 and 2 g/kg/day icosapent ethyl from gestation through organogenesis all drug treated groups had non-dose-related imbalances in visceral and skeletal findings, including 13th reduced ribs, additional liver lobes, testes medially displaced and/or not descended, at human systemic exposures following a maximum oral dose of 4 g/day based on body surface comparisons.

In a multigenerational developmental study in pregnant rats given doses of 0.3, 1, 3 g/kg/day icosapent ethyl by oral gavage from gestation day 7-17, icosapent ethyl did not affect viability in fetuses (F1 or F2). Non-dose-related imbalances in findings of absent optic nerves and unilateral testes atrophy at human exposures based on the maximum dose of 4 g/day and on body surface area comparisons. Additional variations consisting of early incisor eruption and increased percent cervical ribs were observed at the same exposures. Pups from high dose treated dams exhibited decreased copulation rates, delayed estrus, decreased implantations and decreased surviving fetuses (F2) suggesting potential multigenerational effects of icosapent ethyl at 7 times human systemic exposure following 4 g/day dose based on body surface area comparisons across species.

In pregnant rabbits given oral gavage doses of 0.1, 0.3, and 1 g/kg/day icosapent ethyl from gestation through organogenesis, a decrease in body weight and food consumption was observed at the high dose of 1 g/kg/day (5 times the human exposure at the maximum dose of 4 g/day, based on body surface area comparisons). Slight increases in resorbed and dead fetuses were noted in the 1 g/kg/day group, but these were not significantly different from the control group. There were no differences between the icosapent ethyl groups and control group as to the number of corpora lutea, number of implantations, number of surviving fetuses, sex ratio, body weight of female fetuses or placental weight. There were no treatment-related malformations or skeletal anomalies.

In pregnant rats given icosapent ethyl from gestation day 17 through lactation day 20 at 0.3, 1, 3 g/kg/day no adverse maternal or developmental effects were observed. However, complete litter loss (not dose-related) was noted in 2/23 litters at the low dose and 1/23 mid-dose dams by post-natal day 4 at human exposures at a maximum dose of 4 g/day, based on body surface area comparisons.

8.2 Lactation

Risk Summary

Published studies have detected omega-3 fatty acids, including EPA, in human milk. Lactating women receiving oral omega-3 fatty acids for supplementation have resulted in higher levels of omega-3 fatty acids in human milk. There are no data on the effects of omega-3 fatty acid ethyl esters on the breastfed infant or on milk production. The developmental and health benefits of breastfeeding should be considered along with the mother’s clinical need for VASCEPA and any potential adverse effects on the breastfed child from VASCEPA or from the underlying maternal condition.

8.4 Pediatric Use

Safety and effectiveness in pediatric patients have not been established.

8.5 Geriatric Use

Of the total number of patients in well-controlled clinical studies of VASCEPA, 45% were 65 years of age and over. No overall differences in safety or effectiveness were observed between these patients and younger groups. Other reported clinical experience has not identified differences in responses between the elderly and younger patients.

8.7 Hepatic Impairment

In patients with hepatic impairment, alanine aminotransferase (ALT) and aspartate aminotransferase (AST) levels should be monitored periodically during therapy with VASCEPA.

11 DESCRIPTION

VASCEPA, a lipid-regulating agent, is supplied as either a 0.5 gram or a 1 gram amber-colored, liquid-filled soft gelatin capsule for oral use.

Each VASCEPA capsule contains either 0.5 grams of icosapent ethyl (in a 0.5 gram capsule) or 1 gram of icosapent ethyl (in a 1 gram capsule). Icosapent ethyl is an ethyl ester of the omega-3 fatty acid eicosapentaenoic acid (EPA). The empirical formula of icosapent ethyl is C22H34O2 and the molecular weight is 330.51. The chemical name for icosapent ethyl is ethyl all-cis-5,8,11,14,17-icosapentaenoate with the following chemical structure:

VASCEPA capsules also contain the following inactive ingredients: tocopherol, gelatin, glycerin, maltitol, sorbitol, and purified water.

12 CLINICAL PHARMACOLOGY

12.1 Mechanism of Action

Studies suggest that EPA reduces hepatic very low-density lipoprotein triglycerides (VLDL-TG) synthesis and/or secretion and enhances TG clearance from circulating VLDL particles. Potential mechanisms of action include increased β-oxidation; inhibition of acyl-CoA:1,2-diacylglycerol acyltransferase (DGAT); decreased lipogenesis in the liver; and increased plasma lipoprotein lipase activity.

The mechanisms of action contributing to reduction of cardiovascular events with VASCEPA (icosapent ethyl) are not completely understood but are likely multi-factorial. Increased EPA lipid composition from carotid plaque specimens and increased circulating EPA/arachidonic acid ratio have been observed following EPA treatment. EPA inhibits platelet aggregation under some ex vivo conditions. However, the direct clinical meaning of individual findings is not clear.

12.2 Pharmacodynamics

In a 12-week, dose-ranging study in patients with severe hypertriglyceridemia and in the event-driven REDUCE-IT® trial, VASCEPA 4 grams per day reduced median TG from baseline relative to placebo [see Clinical Studies (14)].

12.3 Pharmacokinetics

Absorption

After oral administration, VASCEPA is de-esterified during the absorption process and the active metabolite EPA is absorbed in the small intestine and enters the systemic circulation mainly via the thoracic duct lymphatic system. Peak plasma concentrations of EPA were reached approximately 5 hours following oral doses of VASCEPA.

VASCEPA was administered with or following a meal in all clinical studies; no food effect studies were performed. Take VASCEPA with or following a meal.

Distribution

The mean volume of distribution at steady state of EPA is approximately 88 liters. The majority of EPA circulating in plasma is incorporated in phospholipids, triglycerides and cholesteryl esters, and <1% is present as the unesterified fatty acid. Greater than 99% of unesterified EPA is bound to plasma proteins.

Elimination

Metabolism

EPA is mainly metabolized by the liver via beta-oxidation similar to dietary fatty acids. Beta oxidation splits the long carbon chain of EPA into acetyl Coenzyme A, which is converted into energy via the Krebs cycle. Cytochrome P450-mediated metabolism is a minor pathway of elimination of EPA.

Excretion

The total plasma clearance of EPA at steady state is 684 mL/hr. The plasma elimination half-life (t1/2) of EPA is approximately 89 hours. VASCEPA does not undergo renal excretion.

Specific Populations

Gender

When administered VASCEPA in clinical trials, plasma total EPA concentrations did not differ significantly between men and women.

Pediatric

The pharmacokinetics of VASCEPA have not been studied in pediatric patients.

Hepatic or Renal Impairment

VASCEPA has not been studied in patients with renal or hepatic impairment.

Drug Interaction Studies

Omeprazole

In a drug-drug interaction study with 28 healthy adult subjects, VASCEPA 4 g/day at steady-state did not significantly change the steady-state AUCτ or Cmax of omeprazole when co-administered at 40 mg/day to steady-state.

Rosiglitazone

In a drug-drug interaction study with 28 healthy adult subjects, VASCEPA 4 g/day at steady-state did not significantly change the single dose AUC or Cmax of rosiglitazone at 8 mg.

Warfarin

In a drug-drug interaction study with 25 healthy adult subjects, VASCEPA 4 g/day at steady-state did not significantly change the single dose AUC or Cmax of R- and S-warfarin or the anti-coagulation pharmacodynamics of warfarin when co-administered as racemic warfarin at 25 mg.

Atorvastatin

In a drug-drug interaction study of 26 healthy adult subjects, VASCEPA 4 g/day at steady-state did not significantly change the steady-state AUCτ or Cmax of atorvastatin, 2-hydroxyatorvastatin, or 4-hydroxyatorvastatin when co-administered with atorvastatin 80 mg/day at steady-state.

13 NONCLINICAL TOXICOLOGY

13.1 Carcinogenesis, Mutagenesis, Impairment of Fertility

In a 2-year rat carcinogenicity study with oral gavage doses of 0.09, 0.27, and 0.91 g/kg/day icosapent ethyl, respectively, males did not exhibit drug-related neoplasms. Hemangiomas and hemangiosarcomas of the mesenteric lymph node, the site of drug absorption, were observed in females at clinically relevant exposures based on body surface area comparisons across species relative to the maximum clinical dose of 4 g/day. Overall incidence of hemangiomas and hemangiosarcomas in all vascular tissues did not increase with treatment.

In a 6-month carcinogenicity study in Tg.rasH2 transgenic mice with oral gavage doses of 0.5, 1, 2, and 4.6 g/kg/day icosapent ethyl, drug-related incidences of benign squamous cell papilloma in the skin and subcutis of the tail was observed in high dose male mice. The papillomas were considered to develop secondary to chronic irritation of the proximal tail associated with fecal excretion of oil and therefore not clinically relevant. Drug-related neoplasms were not observed in female mice.

Icosapent ethyl was not mutagenic with or without metabolic activation in the bacterial mutagenesis (Ames) assay or in the in vivo mouse micronucleus assay. A chromosomal aberration assay in Chinese Hamster Ovary (CHO) cells was positive for clastogenicity with and without metabolic activation.

In an oral gavage rat fertility study, ethyl-EPA, administered at doses of 0.3, 1, and 3 g/kg/day to male rats for 9 weeks before mating and to female rats for 14 days before mating through day 7 of gestation, increased anogenital distance in female pups and increased cervical ribs were observed at 3 g/kg/day (7 times human systemic exposure with 4 g/day clinical dose based on a body surface area comparison).

14 CLINICAL STUDIES

14.1 Prevention of Cardiovascular Events

REDUCE-IT (NCT01492361) was a multinational, double-blind, randomized, placebo-controlled, event-driven trial in 8,179 (4,089 VASCEPA, 4,090 placebo) statin-treated adult patients enrolled with LDL-C >40 mg/dL and ≤100 mg/dL and elevated TG levels (90% of enrolled patients had TG ≥ 150 mg/dL and <500 mg/dL) and either established cardiovascular disease (71%) or diabetes and other risk factors for cardiovascular disease (29%). Patients with established cardiovascular disease were defined as being at least 45 years of age and having a documented history of coronary artery disease, cerebrovascular or carotid disease, or peripheral artery disease. Patients with other risk factors for cardiovascular disease were defined as being at least 50 years of age with diabetes and at least one additional risk factor. Patients were randomly assigned 1:1 to receive either VASCEPA (4 grams daily) or placebo. The median follow-up duration was 4.9 years. Overall, 99.8% of patients were followed for vital status until the end of the trial or death.

The median age at baseline was 64 years and 29% were women. The trial population was 90% White, 5% Asian, 2% Black; 4% identified as Hispanic ethnicity. Selected additional baseline risk factors included hypertension (87%), type 2 diabetes mellitus (58%), eGFR < 60 mL/min per 1.73 m^2 (22%), congestive heart failure (18%), and current daily cigarette smoking (15%).

Most patients were taking moderate-intensity (63%) or high-intensity (31%) statin therapy at baseline. Most patients at baseline were taking at least one other cardiovascular medication, including anti-platelet agents (79%) or anti-hypertensives (95%), including beta blockers (71%), angiotensin converting enzyme (ACE) inhibitors (52%), or angiotensin receptor blockers (ARB; 27%).

On stable background lipid-lowering therapy, the median [Q1, Q3] LDL-C at baseline was 75.0 [62.0, 89.0] mg/dL; the mean (SD) was 76.2 (20.3) mg/dL. The median [Q1, Q3] fasting TG was 216.0 [176.0, 272.5] mg/dL; the mean (SD) was 233.2 (80.1) mg/dL.

VASCEPA significantly reduced the risk for the primary composite endpoint (time to first occurrence of cardiovascular death, myocardial infarction, stroke, coronary revascularization, or hospitalization for unstable angina; p<0.0001) and the key secondary composite endpoint (time to first occurrence of cardiovascular death, myocardial infarction, or stroke; p<0.0001). The results of the primary, key secondary, and other secondary efficacy endpoints in the prespecified testing hierarchy to control for type 1 error are shown in Table 1. The Kaplan-Meier estimates of the cumulative incidence of the primary composite endpoints over time are shown in Figure 1.

Table 1. Effect of VASCEPA on Time to First Occurrence of Cardiovascular Events in Patients with Elevated Triglyceride Levels and Other Risk Factors for Cardiovascular Disease in REDUCE-IT
 | VASCEPA |  | Placebo |  | VASCEPA vs Placebo
 | N = 4089 n (%) | Incidence Rate (per 100 patient years) | N = 4090 n (%) | Incidence Rate (per 100 patient years) | Hazard Ratio (95% CI)
Primary composite endpoint
Cardiovascular death, myocardial infarction, stroke, coronary revascularization, hospitalization for unstable angina (5-point MACE) | 705 (17.2) | 4.3 | 901 (22.0) | 5.7 | 0.75 (0.68, 0.83)
Key secondary composite endpoint
Cardiovascular death, myocardial infarction, stroke (3-point MACE) | 459 (11.2) | 2.7 | 606 (14.8) | 3.7 | 0.74 (0.65, 0.83)
Other secondary endpoints
Fatal or non-fatal myocardial infarction | 250 (6.1) | 1.5 | 355 (8.7) | 2.1 | 0.69 (0.58, 0.81)
Emergent or urgent coronary revascularization | 216 (5.3) | 1.3 | 321 (7.8) | 1.9 | 0.65 (0.55, 0.78)
Cardiovascular death [1] | 174 (4.3) | 1.0 | 213 (5.2) | 1.2 | 0.80 (0.66, 0.98)
Hospitalization for unstable angina [2] | 108 (2.6) | 0.6 | 157 (3.8) | 0.9 | 0.68 (0.53, 0.87)
Fatal or non-fatal stroke | 98 (2.4) | 0.6 | 134 (3.3) | 0.8 | 0.72 (0.55, 0.93)
[1] Includes adjudicated cardiovascular deaths and deaths of undetermined causality.
[2] Determined to be caused by myocardial ischemia by invasive/non-invasive testing and requiring emergent hospitalization.

Figure 1. Kaplan-Meier Estimated Cumulative Incidence of Primary Composite Endpoint in REDUCE-IT

CI=confidence interval

The median TG and LDL-C baseline values were similar between the VASCEPA group and placebo group. The median change in TG from baseline to Year 1 was -39 mg/dL (-18%) in the VASCEPA group and 5 mg/dL (2%) in the placebo group. The median change in LDL-C from baseline to Year 1 was 2 mg/dL (3%) in the VASCEPA group and 7 mg/dL (10%) in the placebo group.

14.2 Severe Hypertriglyceridemia

The effects of VASCEPA 4 grams per day were assessed in a randomized, placebo-controlled, double-blind, parallel-group study of adult patients (76 on VASCEPA, 75 on placebo) with severe hypertriglyceridemia. Patients whose baseline TG levels were between 500 and 2,000 mg/dL were enrolled in this study for 12 weeks. The median baseline TG and LDL-C levels in these patients were 684 mg/dL and 86 mg/dL, respectively. Median baseline HDL-C level was 27 mg/dL. The randomized population in this study was mostly Caucasian (88%) and male (76%). The mean age was 53 years and the mean body mass index was 31 kg/m^2. Twenty-five percent of patients were on concomitant statin therapy, 28% were diabetics, and 39% of the patients had TG levels >750 mg/dL.

The changes in the major lipoprotein lipid parameters for the groups receiving VASCEPA or placebo are shown in Table 2.

Table 2. Median Baseline and Percent Change from Baseline in Lipid Parameters in Patients with Severe Hypertriglyceridemia (≥500 mg/dL)
Parameter | VASCEPA 4 g/day N=76 |  | Placebo N=75 |  | Difference (95% Confidence Interval)
Parameter | Baseline | % Change | Baseline | % Change | Difference (95% Confidence Interval)
TG (mg/dL) | 680 | -27 | 703 | +10 | -33* (-47, -22)
LDL-C (mg/dL) | 91 | -5 | 86 | -3 | -2 (-13, +8)
Non-HDL-C (mg/dL) | 225 | -8 | 229 | +8 | -18 (-25, -11)
TC (mg/dL) | 254 | -7 | 256 | +8 | -16 (-22, -11)
HDL-C (mg/dL) | 27 | -4 | 27 | 0 | -4 (-9, +2)
VLDL-C (mg/dL) | 123 | -20 | 124 | +14 | -29** (-43, -14)
Apo B (mg/dL) | 121 | -4 | 118 | +4 | -9** (-14, -3)
% Change= Median Percent Change from Baseline
Difference= Median of [VASCEPA % Change – Placebo % Change] (Hodges-Lehmann Estimate)
p-values from Wilcoxon rank-sum test
*p-value < 0.001 (primary efficacy endpoint)
**p-value < 0.05 (key secondary efficacy endpoints determined to be statistically significant according to the pre-specified multiple comparison procedure)

VASCEPA 4 grams per day reduced median TG, VLDL-C, and Apo B levels from baseline relative to placebo. The reduction in TG observed with VASCEPA was not associated with elevations in LDL-C levels relative to placebo.

16 HOW SUPPLIED/STORAGE AND HANDLING

VASCEPA (icosapent ethyl) capsules are supplied as

Strength | Quantity | Description | NDC
0.5 gram capsules | Bottles of 240 | amber-colored soft-gelatin capsules imprinted with V500 | 52937-003-40
1 gram capsules | Bottles of 120 | amber-colored soft-gelatin capsules imprinted with VASCEPA | 52937-001-20
1 gram capsules | Bottles of 120 | amber-colored soft-gelatin capsules imprinted with IPE | 52937-005-20

Store at 20° to 25° C (68° to 77°F); excursions permitted to 15° to 30° C (59° to 86°F) [see USP Controlled Room Temperature].

17 PATIENT COUNSELING INFORMATION

Advise the patient to read the FDA-approved patient labeling before starting VASCEPA (Patient Information).

Inform patients that VASCEPA may increase their risk for atrial fibrillation or atrial flutter [see Warnings and Precautions (5.1)].

Inform patients with known hypersensitivity to fish and/or shellfish about the potential for allergic reactions to VASCEPA and advise them to discontinue VASCEPA and seek medical attention if any reactions occur [see Warnings and Precautions (5.2)].

Inform patients that VASCEPA may increase their risk for bleeding, especially if they are receiving other antithrombotic agents [see Warnings and Precautions (5.3)].

Advise patients to swallow VASCEPA capsules whole. Do not break open, crush, dissolve, or chew VASCEPA [see Dosage and Administration (2.2)].

Instruct patients to take VASCEPA as prescribed. If a dose is missed, patients should take it as soon as they remember. However, if they miss one day of VASCEPA, they should not double the dose when they take it.

For more information about VASCEPA, go to www.VASCEPA.com or call 1-855-VASCEPA (1-855-827-2372).

AMARIN®

VASCEPA® (icosapent ethyl)

Distributed by:
Amarin Pharma, Inc.
Bridgewater, NJ, USA

Manufactured for:
Amarin Pharmaceuticals Ireland Limited
Dublin, Ireland

VASCEPA is a registered trademark of the Amarin group of companies

©2025 Amarin Pharma, Inc. Bridgewater NJ 08807. All rights reserved

P00120P 12/2025

PATIENT INFORMATION
VASCEPA® (vas-EE-puh) (icosapent ethyl)
capsules

What is VASCEPA?
VASCEPA is a prescription medicine used:

- along with certain medicines (statins) to reduce the risk of heart attack, stroke, and certain types of heart issues requiring hospitalization in adults with heart (cardiovascular) disease, or diabetes and 2 or more additional risk factors for heart disease.
- along with a low-fat and low-cholesterol diet to lower high levels of triglycerides (fats) in adults.

It is not known if VASCEPA changes your risk of having inflammation of your pancreas (pancreatitis).
It is not known if VASCEPA is safe and effective in children.

Do not take VASCEPA if you are allergic to icosapent ethyl or any of the ingredients in VASCEPA. See the end of this leaflet for a complete list of ingredients in VASCEPA.

Before taking VASCEPA, tell your doctor about all of your medical conditions, including if you:

- have diabetes.
- have a low thyroid problem (hypothyroidism).
- have a liver problem.
- have a pancreas problem.
- are allergic to fish or shellfish. It is not known if people who are allergic to fish or shellfish are also allergic to VASCEPA.
- are pregnant, or planning to become pregnant. It is not known if VASCEPA will harm your unborn baby.
- are breastfeeding or plan to breastfeed. VASCEPA can pass into your breast milk, and may harm your baby. Talk to your doctor about the best way to feed your baby if you take VASCEPA.

Tell your doctor about all the medicines you take, including prescription and over-the-counter medicines, vitamins, and dietary or herbal supplements.
VASCEPA can interact with certain other medicines that you are taking.
Especially tell your doctor if you take medicines that affect your blood clotting (anticoagulants or blood thinners).

How should I take VASCEPA?

- Take VASCEPA exactly as your doctor tells you to take it.
- Do not change your dose or stop taking VASCEPA without talking to your doctor.
- Do not take more capsules than what is prescribed by your doctor.
  - If you are prescribed the 0.5-gram capsules, you should not take more than 8 capsules each day with food.
  - If you are prescribed the 1-gram capsules, you should not take more than 4 capsules each day with food.
- Take VASCEPA capsules whole. Do not break, crush, dissolve, or chew VASCEPA capsules before swallowing.
- If you miss a dose of VASCEPA, take it as soon as you remember. However, if you miss one day of VASCEPA, do not double your dose when you take it.
- Your doctor may start you on a diet that is low in saturated fat, cholesterol, carbohydrates, and low in added sugars before giving you VASCEPA. Stay on this diet while taking VASCEPA.
- Your doctor may do blood tests to check your triglyceride and other lipid levels while you take VASCEPA.

What are the possible side effects of VASCEPA?
VASCEPA may cause serious side effects, including:

- Heart rhythm problems (atrial fibrillation and atrial flutter). Heart rhythm problems which can be serious and cause hospitalization have happened in people who take VASCEPA, especially in people who have heart (cardiovascular) disease or diabetes with a risk factor for heart (cardiovascular) disease, or who have had heart rhythm problems in the past. Tell your doctor if you get any symptoms of heart rhythm problems such as feeling as if your heart is beating fast and irregular, lightheadedness, dizziness, shortness of breath, chest discomfort, or you faint.
- Possible allergic reactions if you are allergic to fish or shellfish. Stop taking VASCEPA and tell your doctor right away or get emergency medical help if you have any signs or symptoms of an allergic reaction.
- Bleeding. Serious bleeding can happen in people who take VASCEPA. Your risk of bleeding may increase if you are also taking a blood thinner medicine.

If you have liver problems and are taking VASCEPA, your doctor should do blood tests during treatment.
The most common side effects of VASCEPA include:

- Muscle and joint pain.
- Swelling of the hands, legs, or feet.
- Constipation
- Gout
- Heart rhythm problems (atrial fibrillation).

These are not all the possible side effects of VASCEPA. Call your doctor for medical advice about side effects. You may report side effects to FDA at 1-800-FDA-1088.

How should I store VASCEPA?

- Store VASCEPA at room temperature between 68° to 77° F (20° to 25° C).
- Safely throw away medicine that is out of date or no longer needed.

Keep VASCEPA and all medicine out of the reach of children.

General information about the safe and effective use of VASCEPA.
Medicines are sometimes prescribed for purposes other than those listed in a Patient Information leaflet. Do not use VASCEPA for a condition for which it was not prescribed. Do not give VASCEPA to other people, even if they have the same symptoms that you have. It may harm them. You can ask your pharmacist or healthcare provider for information about VASCEPA that is written for health professionals.

What are the ingredients in VASCEPA?
Active ingredient: icosapent ethyl
Inactive ingredients: tocopherol, gelatin, glycerin, maltitol, sorbitol, and purified water

VASCEPA is a registered trademark of the Amarin group of companies.

©2025 Amarin Pharma, Inc. Bridgewater NJ, 08807 All rights reserved

PP00120N

Distributed by: Amarin Pharma Inc. Bridgewater, NJ, USA

Manufactured for: Amarin Pharmaceuticals Ireland Limited Dublin, Ireland +1-855-VASCEPA (+1-855-827-2372) www.vascepa.com

For more information, go to www.vascepa.com or call 1-855-VASCEPA (1-855-827-2372).

This Patient Information has been approved by the U.S. Food and Drug Administration

Revised: 12/2025

PRINCIPAL DISPLAY PANEL - 240 Capsule Bottle Label

NDC 52937-003-40

Vascepa®
(icosapent ethyl)
Capsules

0.5 gram

240 capsules

Rx only

PRINCIPAL DISPLAY PANEL - 120 Capsule Bottle Label

NDC 52937-001-20

Vascepa®
(icosapent ethyl)
Capsules

1 gram

120 capsules

Rx only

PRINCIPAL DISPLAY PANEL - 8 Capsule Blister Carton

RX only

NDC 52937-101-08

SAMPLE ONLY • NOT FOR SALE

Vascepa®
(icosapent ethyl)
Capsules
1 gram

PATIENT SAMPLE PACK
Contains 8 Capsules

Please see enclosed full Prescribing Information for more information on VASCEPA®.
Keep out of reach of children.

PRINCIPAL DISPLAY PANEL - 120 Capsule Bottle Label

NDC 52937-005-20

Vascepa®
(icosapent ethyl)
Capsules

1 gram

120 capsules

Rx only